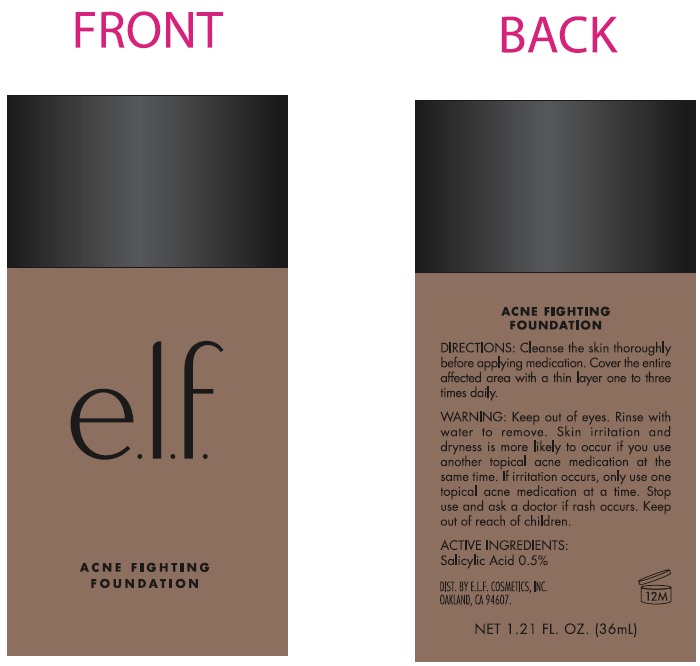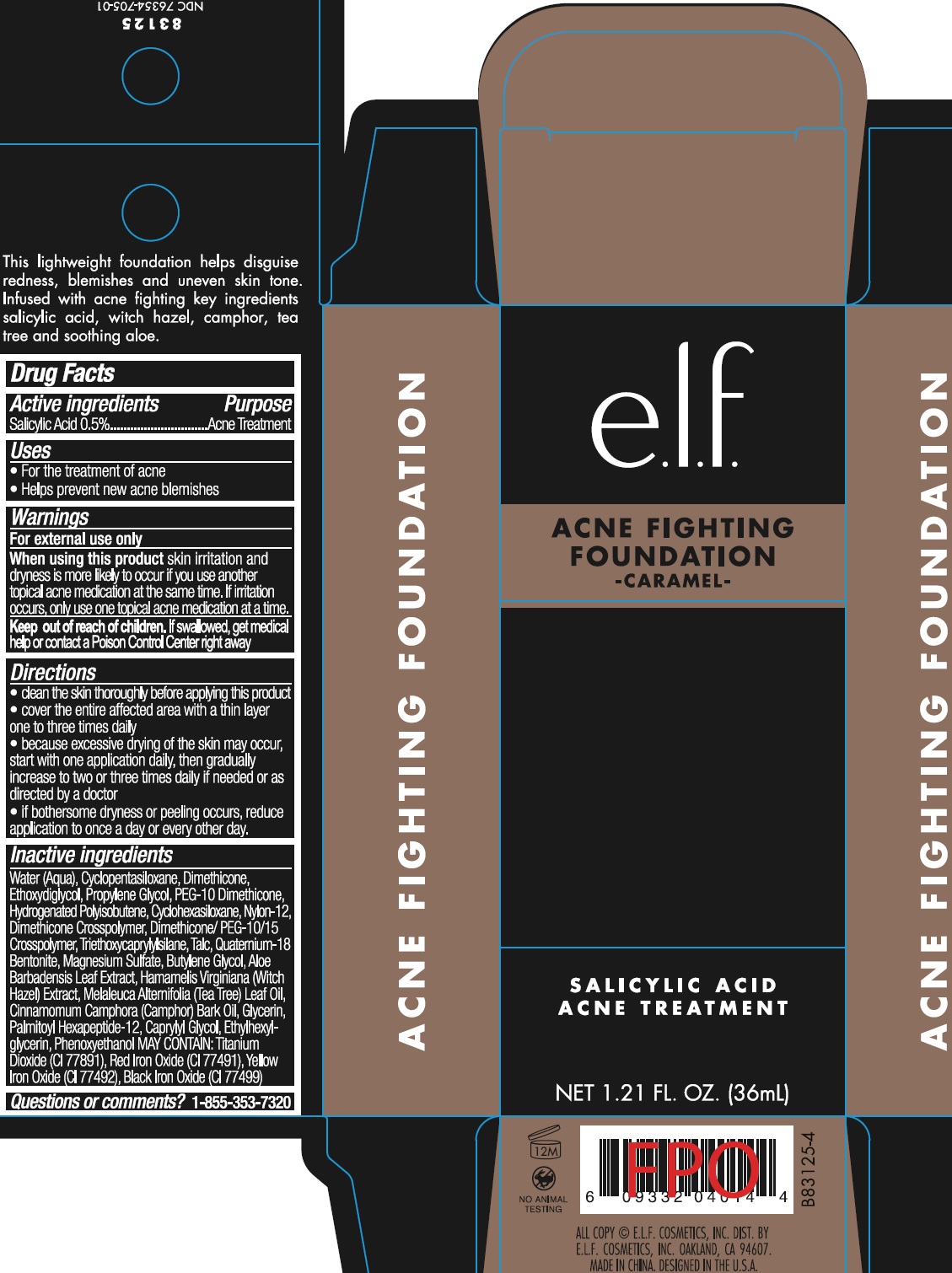 DRUG LABEL: Acne Fighting Foundation Caramel
NDC: 70412-435 | Form: CREAM
Manufacturer: Zhejiang Ayan Biotech Co.,Ltd.
Category: otc | Type: HUMAN OTC DRUG LABEL
Date: 20231106

ACTIVE INGREDIENTS: SALICYLIC ACID 5 mg/1 mL
INACTIVE INGREDIENTS: WATER; CYCLOMETHICONE 5; DIMETHICONE; DIETHYLENE GLYCOL MONOETHYL ETHER; PROPYLENE GLYCOL; PEG-10 DIMETHICONE (600 CST); HYDROGENATED POLYBUTENE (1300 MW); CYCLOMETHICONE 6; NYLON-12; DIMETHICONE CROSSPOLYMER (450000 MPA.S AT 12% IN CYCLOPENTASILOXANE); TRIETHOXYCAPRYLYLSILANE; TALC; BENTOQUATAM; MAGNESIUM SULFATE, UNSPECIFIED FORM; BUTYLENE GLYCOL; ALOE VERA LEAF; WITCH HAZEL; TEA TREE OIL; CAMPHOR OIL; GLYCERIN; PALMITOYL HEXAPEPTIDE-12; CAPRYLYL GLYCOL; ETHYLHEXYLGLYCERIN; PHENOXYETHANOL

Acne Fighting Foundation Caramel

Active ingredients

Salicylic Acid 0.5%

Purpose

Acne Treatment

Uses

- For the treatment of acne
- Helps prevent new acne blemishes

Warnings

For external use only

When using this product

skin irritation and dryness is more likely to occur if you use another topical acne medication at the same time. If irritation occurs, only use one topical acne medication at a time.

Keep out of reach of children.

If swallowed, get medical help or contact a Poison Control Center right away

Directions

- clear the skin thoroughly before applying this product
- cover the entire affected area with a thin layer one to three times daily
- because excessive drying of the skin may occur, start with one application daily, then gradually increase to two or three times daily if needed or as directed by a doctor
- if bothersome dryness or peeling occurs, reduce application to once a day or every other day.

Inactive ingredients

Water (Aqua), Cyclopentasiloxane, Dimethicone, Ethoxydiglycol, Propylene Glycol, PEG-10 Dimethicone, Hydrogenated Polyisobutene, Cyclohexasiloxane, Nylon-12, Dimethicone Crosspolymer, Dimethicone/PEG-10/15 Crosspolymer, Triethoxycaprylylsilane, Talc, Quaternium-18 Bentonite, Magnesium Sulfate, Butylene Glycol, Aloe Barbadensis Leaf Extract, Hamamelis Virginiana (Witch Hazel) Extract, Melaleuca Alternifolia (Tea Tree) Leaf Oil, Cinnamomum Camphora (Camphor) Bark Oil, Glycerin, Palmitoyl Hexapeptide-12, Caprylyl Glycol, Ethylhexylglycerin, Phenoxyethanol, MAY CONTAIN: Titanium Dioxide (CI 77891), Red Iron Oxide (CI 77491), Yellow Iron Oxide (CI 77492), Black Iron Oxide (CI 77499)

Questions or comments?

1-855-353-7320